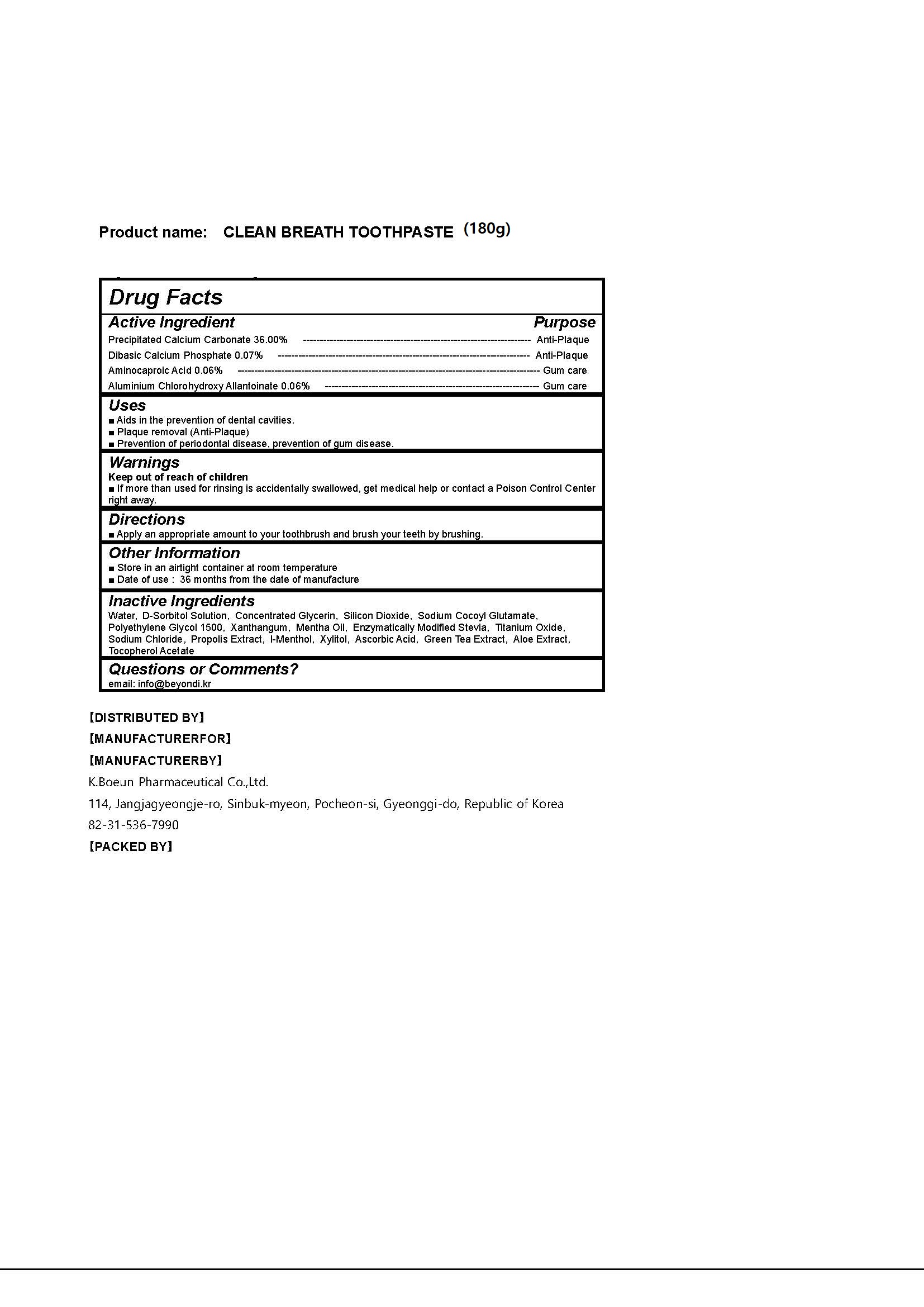 DRUG LABEL: CLEAN BREATH TOOTH
NDC: 74724-0028 | Form: PASTE, DENTIFRICE
Manufacturer: K.Boeun Pharmaceutical Co.,Ltd.
Category: otc | Type: HUMAN OTC DRUG LABEL
Date: 20211130

ACTIVE INGREDIENTS: CALCIUM PHOSPHATE, DIBASIC, ANHYDROUS 0.07 g/100 g; CALCIUM CARBONATE 36 g/100 g; ALCLOXA 0.06 g/100 g; AMINOCAPROIC ACID 0.06 g/100 g
INACTIVE INGREDIENTS: XYLITOL; WATER

ACTIVE INGREDIENT

Precipitated Calcium Carbonate, Dibasic Calcium Phosphate, Aminocaproic Acid, Aluminium Chlorohydroxy Allantoinate

INACTIVE INGREDIENT

Water, D-Sorbitol Solution, Concentrated Glycerin, Silicon Dioxide, Sodium Cocoyl Glutamate, Polyethylene Glycol 1500, Xanthangum, Mentha Oil, Enzymatically Modified Stevia, Titanium Oxide, Sodium Chloride, Propolis Extract, l-Menthol, Xylitol, Ascorbic Acid, Green Tea Extract, Aloe Extract, Tocopherol Acetate

PURPOSE

For dental care

Keep out of reach of children

INDICATIONS AND USAGE

Apply an appropriate amount to your toothbrush and brush your teeth by brushing.

Warnings

Keep out of reach of children

■ If more than used for rinsing is accidentally swallowed, get medical help or contact a Poison Control Center right away.

Other Information

■ Store in an airtight container at room temperature

■ Date of use : 36 months from the date of manufacture

DOSAGE AND ADMINISTRATION

For dental use only